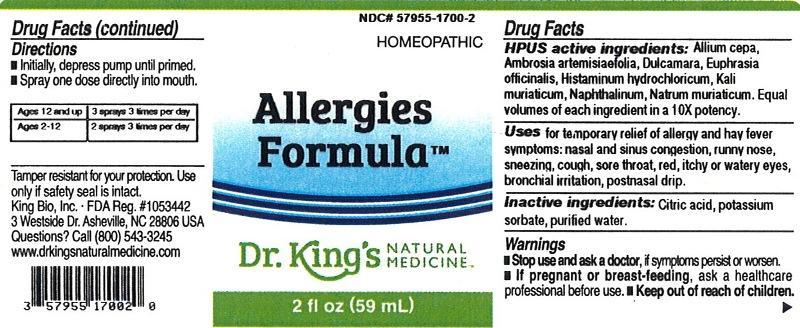 DRUG LABEL: Allergies Formula
NDC: 57955-1700 | Form: LIQUID
Manufacturer: King Bio Inc.
Category: homeopathic | Type: HUMAN OTC DRUG LABEL
Date: 20140131

ACTIVE INGREDIENTS: ONION 10 [hp_X]/59 mL; AMBROSIA ARTEMISIIFOLIA 10 [hp_X]/59 mL; SOLANUM DULCAMARA TOP 10 [hp_X]/59 mL; EUPHRASIA STRICTA 10 [hp_X]/59 mL; HISTAMINE DIHYDROCHLORIDE 10 [hp_X]/59 mL; POTASSIUM CHLORIDE 10 [hp_X]/59 mL; NAPHTHALENE 10 [hp_X]/59 mL; SODIUM CHLORIDE 10 [hp_X]/59 mL
INACTIVE INGREDIENTS: CITRIC ACID MONOHYDRATE; POTASSIUM SORBATE; WATER

Allergies Formula

Drug Facts

____________________________________________________________________________________________________________________

HPUS active ingredients: Allium cepa, Ambrosia artemisiaefolia, Dulcamara, Euphrasia officinalis, Histaminum hydrochloricum, Kali muriaticum, Naphthalinum, Natrum muriaticum. Equal volumes of each ingredient in a 10X potency.

INDICATIONS AND USAGE

Uses for temporary relief of allergy and hay fever symptoms: nasal and sinus congestion, runny nose, sneezing, cough, sore throat, red, itchy or watery eyes, bronchial irritation, postnasal drip.

Inactive ingredients: Citric acid, potassium sorbate, purified water.

Warnings

- Stop use and ask your doctor, if symptoms persist or worsen.
- If pregnant or breast-feeding, ask a healthcare professional before use.

- Keep out of reach of children.

Directions:

- Initially, depress pump until primed.
- Spray one dose directly into mouth.
- Ages 12 and up: 3 sprays 3 times per day.
- Ages 2-12: 2 sprays 3 times per day.

OTHER SAFETY INFORMATION

Tamper resistant for your protection. Use only if safety seal is intact.

PURPOSE

Uses for temporary relief of allergy and hay fever symptoms:

- nasal and sinus congestion
- runny nose
- sneezing
- cough
- sore throat
- red, itchy or watery eyes
- bronchial irritation
- postnasal drip